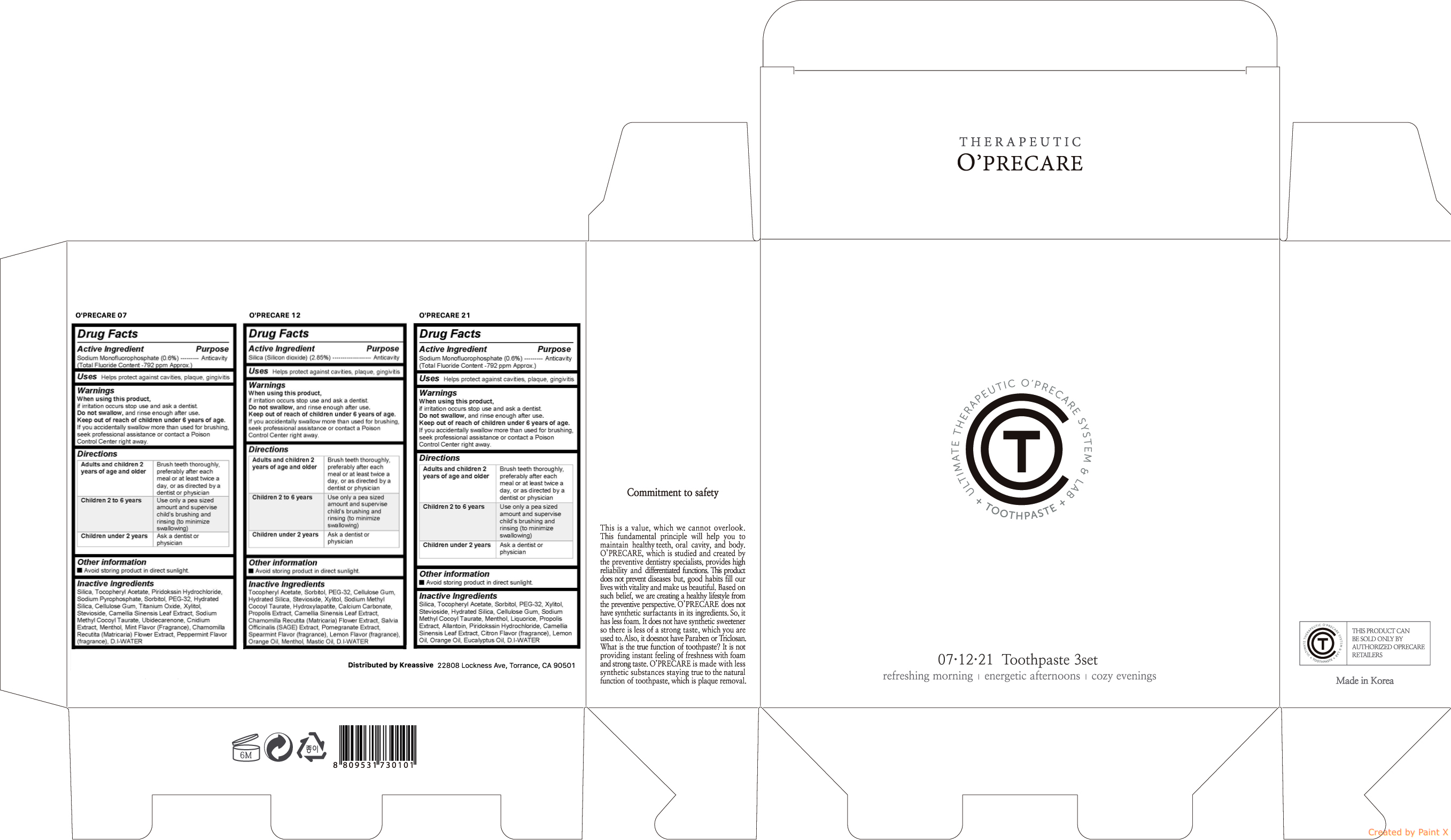 DRUG LABEL: OPRECARE 3SET (07,12,21)
NDC: 71764-104 | Form: KIT | Route: DENTAL
Manufacturer: O'PRECARE
Category: otc | Type: HUMAN OTC DRUG LABEL
Date: 20171012

ACTIVE INGREDIENTS: SODIUM MONOFLUOROPHOSPHATE 0.36 g/60 g; SILICON DIOXIDE 1.71 g/60 g; SODIUM MONOFLUOROPHOSPHATE 0.36 g/60 g
INACTIVE INGREDIENTS: SILICON DIOXIDE; CARBOXYMETHYLCELLULOSE SODIUM, UNSPECIFIED FORM; XYLITOL; MENTHOL; SODIUM METHYL COCOYL TAURATE; GREEN TEA LEAF; UBIDECARENONE; SODIUM PYROPHOSPHATE; SORBITOL; HYDRATED SILICA; TITANIUM DIOXIDE; STEVIOSIDE; POLYETHYLENE GLYCOL 1500; .ALPHA.-TOCOPHEROL ACETATE; CHAMOMILE; .ALPHA.-TOCOPHEROL ACETATE; SORBITOL; POLYETHYLENE GLYCOL 1500; CARBOXYMETHYLCELLULOSE SODIUM, UNSPECIFIED FORM; HYDRATED SILICA; STEVIOSIDE; Xylitol; SODIUM METHYL COCOYL TAURATE; TRIBASIC CALCIUM PHOSPHATE; Calcium Carbonate; PROPOLIS WAX; GREEN TEA LEAF; CHAMOMILE; SALVIA OFFICINALIS ROOT; POMEGRANATE; ORANGE OIL; Menthol; SILICON DIOXIDE; .ALPHA.-TOCOPHEROL ACETATE; SORBITOL; POLYETHYLENE GLYCOL 1500; Xylitol; Stevioside; Hydrated Silica; CARBOXYMETHYLCELLULOSE SODIUM, UNSPECIFIED FORM; SODIUM METHYL COCOYL TAURATE; Menthol; LICORICE; PROPOLIS WAX; Allantoin; PIRIDOCAINE HYDROCHLORIDE; GREEN TEA LEAF; Lemon Oil; Orange Oil; Eucalyptus Oil

O'PRECARE TOOTHPASTE 3SET (07,12,21)

Active ingredient

Active ingredients
O'PRECARE 07 | Sodium Monofluorophosphate (0.6%)
O'PRECARE 12 | Silica (Silicon dioxide) (2.85%)
O'PRECARE 21 | Sodium Monofluorophosphate (0.6%)

Purpose

Anticavity

Warnings

When using this product, if irritation occurs stop use and ask a dentist. Do not swallow, and rinse enough after use. Keep out of reach of children under 6 years of age. If you accidentally swallow more than used for brushing, seek professional assistance or contact a Poison Control Center right away.

Uses

Helps protect against cavities, plaque, gingivitis

Directions

Adults and children 2 years of age and older | Brush teeth thoroughly, preferably after each meal or at least twice a day, or as directed by a dentist or physician
Children 2 to 6 years | Use only a pea sized amount and supervise childs brushing and rinsing (to minimize swallowing)
Children under 2 years | Ask a dentist or physician

Keep out of reach of children under 6 years of age. If you accidentally swallow more than used for brushing, seek professional assistance or contact a Poison Control Center right away.

Inactive ingredients

O'PRECARE 07 | Silica, Tocopheryl Acetate, Piridokssin Hydrochloride, Sodium Pyrophosphate, Sorbitol, PEG-32, Hydrated Silica, Cellulose Gum, Titanium Oxide, Xylitol, Stevioside, Camellia Sinensis Leaf Extract, Sodium Methyl Cocoyl Taurate, Ubidecarenone, Cnidium Extract, Menthol, Mint Flavor (Fragrance), Chamomilla Recutita (Matricaria) Flower Extract, Peppermint Flavor (fragrance), D.I-WATER
O'PRECARE 12 | Tocopheryl Acetate, Sorbitol, PEG-32, Cellulose Gum, Hydrated Silica, Stevioside, Xylitol, Sodium Methyl Cocoyl Taurate, Hydroxylapatite, Calcium Carbonate, Propolis Extract, Camellia Sinensis Leaf Extract, Chamomilla Recutita (Matricaria) Flower Extract, Salvia Officinalis (SAGE) Extract, Pomegranate Extract, Spearmint Flavor (fragrance), Lemon Flavor (fragrance), Orange Oil, Menthol, Mastic Oil, D.I-WATER
O'PRECARE 21 | Silica, Tocopheryl Acetate, Piridokssin Hydrochloride, Sodium Pyrophosphate, Sorbitol, PEG-32, Hydrated Silica, Cellulose Gum, Titanium Oxide, Xylitol, Stevioside, Camellia Sinensis Leaf Extract, Sodium Methyl Cocoyl Taurate, Ubidecarenone, Cnidium Extract, Menthol, Mint Flavor (Fragrance), Chamomilla Recutita (Matricaria) Flower Extract, Peppermint Flavor (fragrance), D.I-WATER